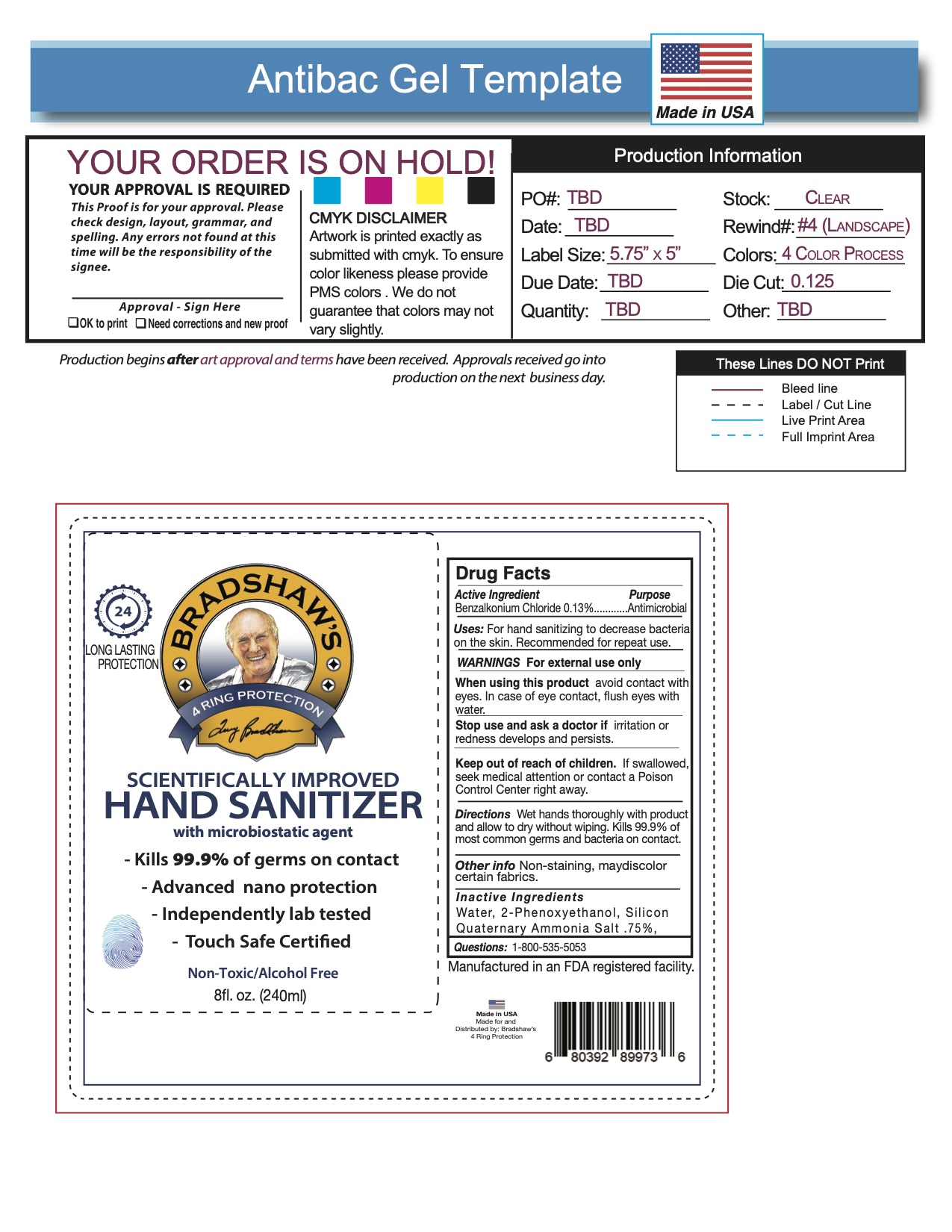 DRUG LABEL: BZK Agent Sanitizer
NDC: 58418-759 | Form: SPRAY
Manufacturer: Tropical Enterprises International, Inc.
Category: otc | Type: HUMAN OTC DRUG LABEL
Date: 20201231

ACTIVE INGREDIENTS: BENZALKONIUM CHLORIDE 0.13 g/30 mL
INACTIVE INGREDIENTS: OCTADECYLDIMETHYL(3-TRIHYDROXYSILYLPROPYL)AMMONIUM CHLORIDE; PHENOXYETHANOL; WATER

Non-Alcohol Sanitizer spray with Spar Additive.

Active Ingredient: Benzalkonium Chloride 0.13%

Stop use and ask a doctor if irritation or redness develops and persists.

Keep out of reach of children. If swallowed, seek medical attention or contact a Poison Control Center right away.

PURPOSE

Uses: For hand sanitizing to decrease bacteria on the skin. Recommended for repeat use.

Questions: 1-800-535-5053

Stop use and ask a doctor if irritation or redness develops and persists.

When using this product avoid contact with eyes. In case of eye contact, flush eyes with water.

DOSAGE AND ADMINISTRATION

Uses: For hand sanitizing to decrease bacteria on the skin. Recommended for repeated use.

Directions: Wet hands thoroughly with product and allow to dry without wiping.

INACTIVE INGREDIENT

Inactive Ingredients: Water, 2-Phenoxyethanol, Silicon Quaternary Ammonia Salt .75%

WARNINGS For external use only

When using this product avoid contact with eyes. In case of eye contact, flush eyes with water.

Other info: Non-staining, may discolor certain fabrics.

INDICATIONS AND USAGE

Uses: For hand sanitizing to decrease bacteria on the skin. Recommended for repeat use.

Directions: Wet hands thoroughly with product and allow to dry without wiping.